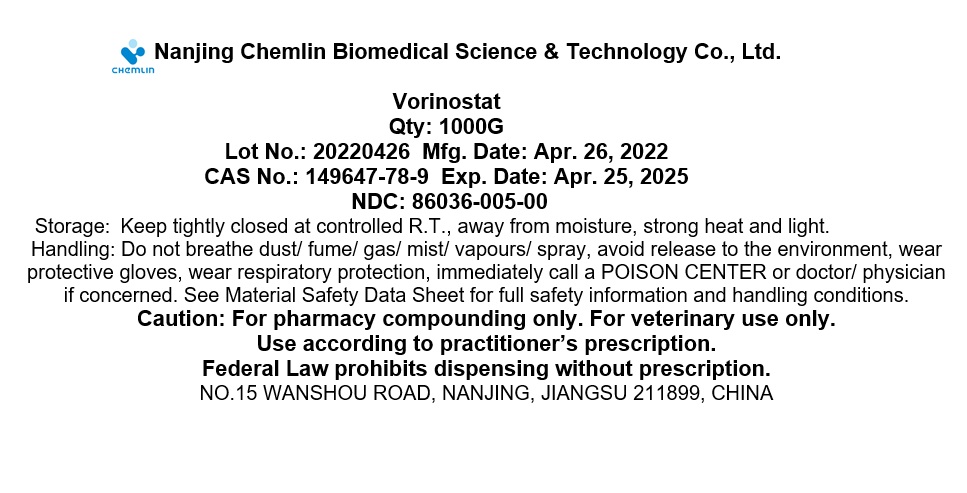 DRUG LABEL: Vorinostat
NDC: 86036-005 | Form: POWDER
Manufacturer: Nanjing Chemlin Biomedical Science & Technology Co, Ltd.
Category: other | Type: BULK INGREDIENT - ANIMAL DRUG
Date: 20240821

ACTIVE INGREDIENTS: VORINOSTAT 1 g/1 g

Vorinostat